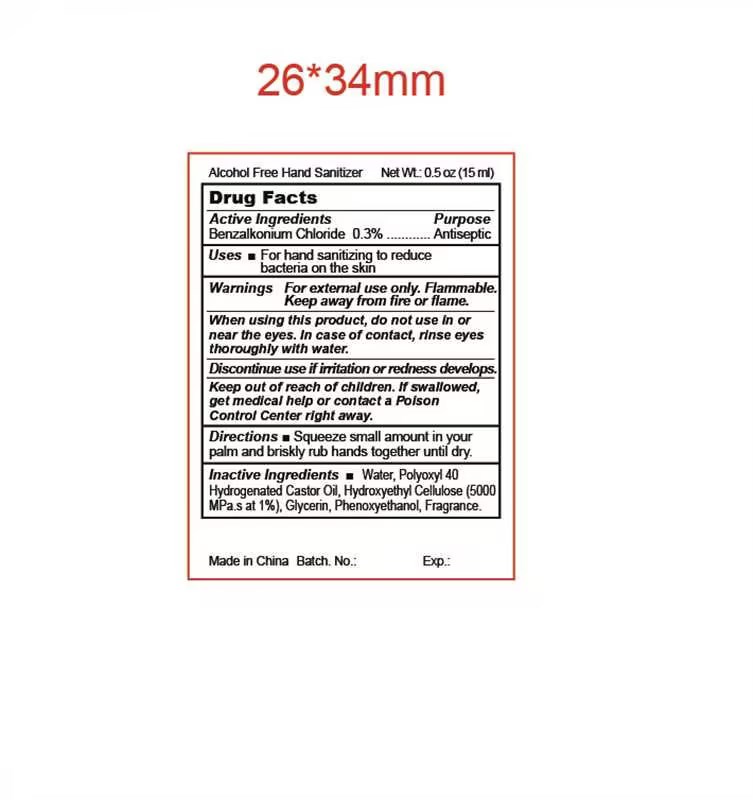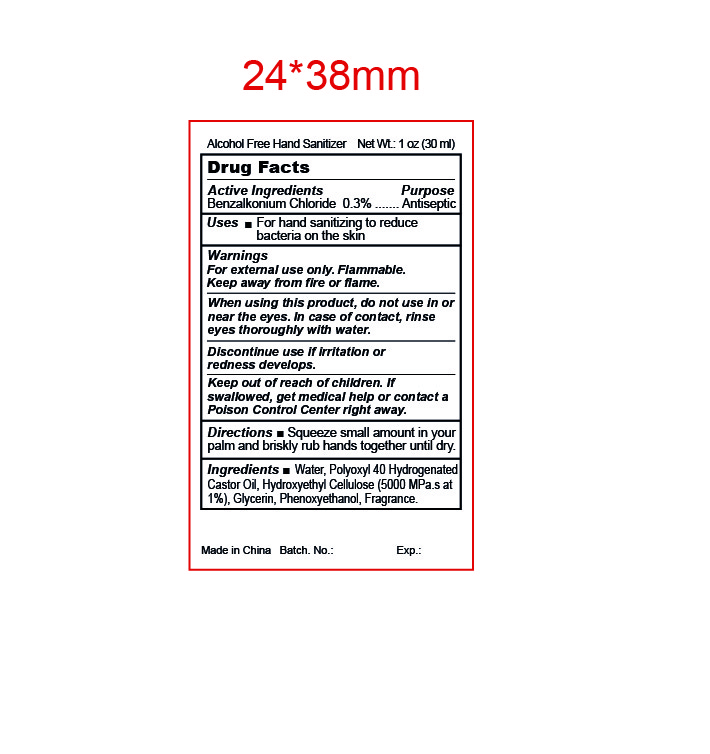 DRUG LABEL: Alcohol Free Hand Sanitizer
NDC: 47993-366 | Form: GEL
Manufacturer: NINGBO JIANGBEI OCEAN STAR TRADING CO.,LTD
Category: otc | Type: HUMAN OTC DRUG LABEL
Date: 20240818

ACTIVE INGREDIENTS: BENZALKONIUM CHLORIDE 0.3 g/100 mL
INACTIVE INGREDIENTS: WATER; POLYOXYL 40 HYDROGENATED CASTOR OIL; HYDROXYETHYL CELLULOSE (5000 MPA.S AT 1%); GLYCERIN; PHENOXYETHANOL

47993-366

Active ingredients

Benzalkonium Chloride 0.3%

PURPOSE

Antiseptic

Uses：

For hand sanitizing to reduce bacteria on the skin.

Warnings:

For external use only.

Flammable. Keep away from fire and flame.

When using this product，do not use in or near the eyes.In case of contact，rinse eyes thoroughly with water.

Discontinue use if irritation or redness develops.

Keep out of reach of children.If swallowed，get medical help or contact a Poison Control Center right away.

Directions:

Squeeze small amount in your palm and briskly rub hands together until dry.

Inactive Ingredients:

Water, Polyoxyl 40 Hydrogenated Castor Oil, Hydroxyethyl Cellulose (5000 Mpa.S At 1%), Glycerin, Phenoxyethanol, Fragrance.